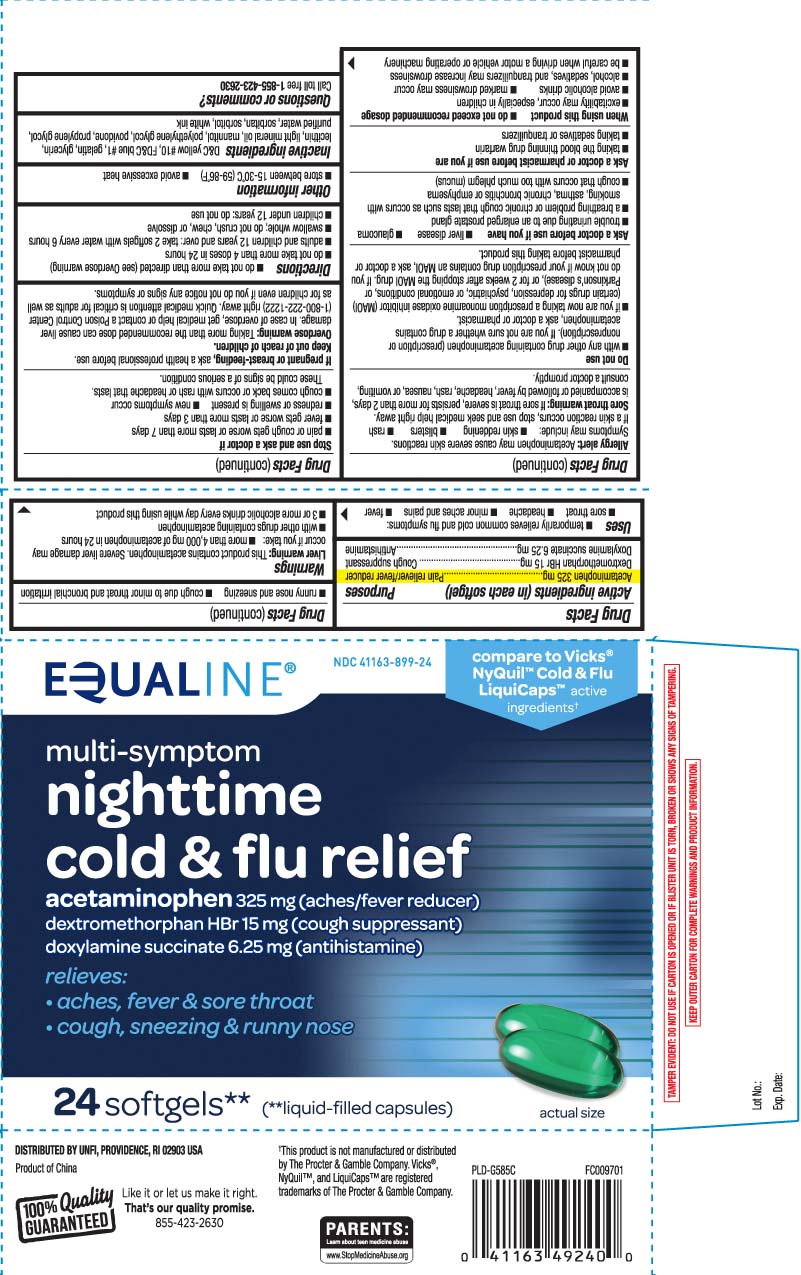 DRUG LABEL: Nighttime Cold and Flu Relief
NDC: 41163-899 | Form: CAPSULE, LIQUID FILLED
Manufacturer: United Natural Foods, Inc. dba UNFI
Category: otc | Type: HUMAN OTC DRUG LABEL
Date: 20260212

ACTIVE INGREDIENTS: ACETAMINOPHEN 325 mg/1 1; DEXTROMETHORPHAN HYDROBROMIDE 15 mg/1 1; DOXYLAMINE SUCCINATE 6.25 mg/1 1
INACTIVE INGREDIENTS: D&C YELLOW NO. 10; FD&C BLUE NO. 1; GELATIN; GLYCERIN; POLYETHYLENE GLYCOL, UNSPECIFIED; POVIDONE; PROPYLENE GLYCOL; WATER; SORBITAN; SORBITOL; MANNITOL; LECITHIN, SOYBEAN; LIGHT MINERAL OIL

Safeway Nighttime Cold & Flu

Active Ingredients (in each softgel)

Acetaminophen 325 mg

Dextromethorphan HBr 15 mg

Doxylamine Succinate 6.25 mg

Purpose

Pain reliever/fever reducer

Cough suppressant

Antihistimine

Purpose

Pain reliever / fever reducer

Cough suppressant

Antihistamine

Uses

- temporarily relieves common cold and flu symptoms:
  - sore throat
  - headache
  - minor aches and pains
  - fever
  - runny nose and sneezing
  - cough due to minor throat and bronchial irritation

Warnings

Liver warning: This product contains acetaminophen. Severe liver damage may occur if you take:

- more than 4,000 mg of acetaminophen in 24 hours
- with other drugs containing acetaminophen
- 3 or more alcoholic drinks every day while using this product

Allergy alert: Acetaminophen may cause severe skin reactions. Symptoms may include:

- Skin reddening
- blisters
- rash

If a skin reaction occurs, stop use and seek medical help right away.

Sore throat warning: If sore throat is severe, persists for more than 2 days, is accompanied or followed by fever, headache, rash, nausea, or vomiting, consult a doctor promptly.

Do not use

- with any other drug containing acetaminophen (prescription or nonprescription). If you are not sure whether a drug contains acetaminophen, ask a doctor or pharmacist.
- if you are now taking a prescription monoamine oxidase inhibitor (MAOI) (certain drugs for depression, psychiatric or emotional conditions, or Parkinson's disease), or for 2 weeks after stopping the MAOI drug. If you do not know if your prescription drug contains an MAOI, ask a doctor of pharmacist before taking this product.

Ask a doctor before use if you have

- liver disease
- glaucoma
- trouble urinating due to an enlarged prostate gland
- a breathing problem or chronic cough that such as occurs with smoking, asthma, chronic bronchitis, or emphysema
- cough that occurs with too much phlegm (mucus)

Ask a doctor of pharmacist before use if you are

- taking the blood thinning drug warfarin
- taking sedatives or tranquilizers

When using this product

- do not exceed recommended dosage
- excitability may occur, especially in children
- avoid alcoholic drinks
- marked drowsiness may occur
- alcohol, sedatives, and tranquilizers may increase drowsiness
- be careful when driving a motor vehicle or operating machinery

Stop use and ask a doctor if

- pain or cough gets worse or lasts more than 7 days
- fever gets worse or lasts more than 3 days
- redness or swelling is present
- new symptoms occur
- cough comes back or occurs with rash or headache that lasts.

These could be signs of a serious condition.

If pregnant or breast-feeding,

ask a health professional before use.

Keep out of reach of children.

Overdose warning: Taking more than the recommended dose can cause liver damage. In case of overdose, get medical help or contact a Poison Control Center (1888-222-1222) right away. Quick medical attention is critical for adults as well as for children even if you do not notice any signs or symptoms.

Directions

- do not take more than directed (see Overdose warning)
- do not take more than 4 doses in 24 hours
- adults and children 12 years and over: take 2 softgels with water every 6 hours
- swallow whole; do not crush, chew, or dissolve
- children under 12 years: do not use

Other Information

- store between 15-30ºC (59-86ºF)
- avoid excessive heat

Inactive Ingredients

D&C yellow #10, FD&C blue #1, gelatin, glycerin, lecithin, light mineral oil, mannitol, polyethylene glycol, povidone, propylene glycol, purified water, sorbitan, sorbitol, white ink

Questions or Comments?

Call toll free 1-855-423-2630

Principal Display Panel

compare to Vicks® NyQuil™ Cold & Flu LiquiCaps™ active ingredients†

multi-symptom

nighttime

cold & flu relief

acetaminophen 325 mg (aches / fever reducer

dextromethorphan HBr 15 mg (cough suppressant)

doxylamine succinate 6.25 mg (antihistamine)

relieves:

- aches, fever, sore throat
- cough, sneezing & runny nose

softgels**

(**liquid-filled capsules)

†This product is not manufactured or distributed by The Procter & Gamble Company. Vicks®, NyQuil™, and LiquiCaps™ are registered trademarks of The Procter & Gamble Company

TAMPER EVIDENT: DO NOT USE IF CARTON IS OPENED OR IF BLISTER UNIT IS TORN, BROKEN OR SHOWS ANY SIGNS OF TAMPERING.

KEEP OUTER CARTON FOR COMPLETE WARNINGS AND PRODUCT INFORMATION.

DISTRIBUTED BY UNFI, PROVIDENCE,RI 02908 USA

Package Label

EQUALINE Multi-Symptom Nighttime Cold & Flu